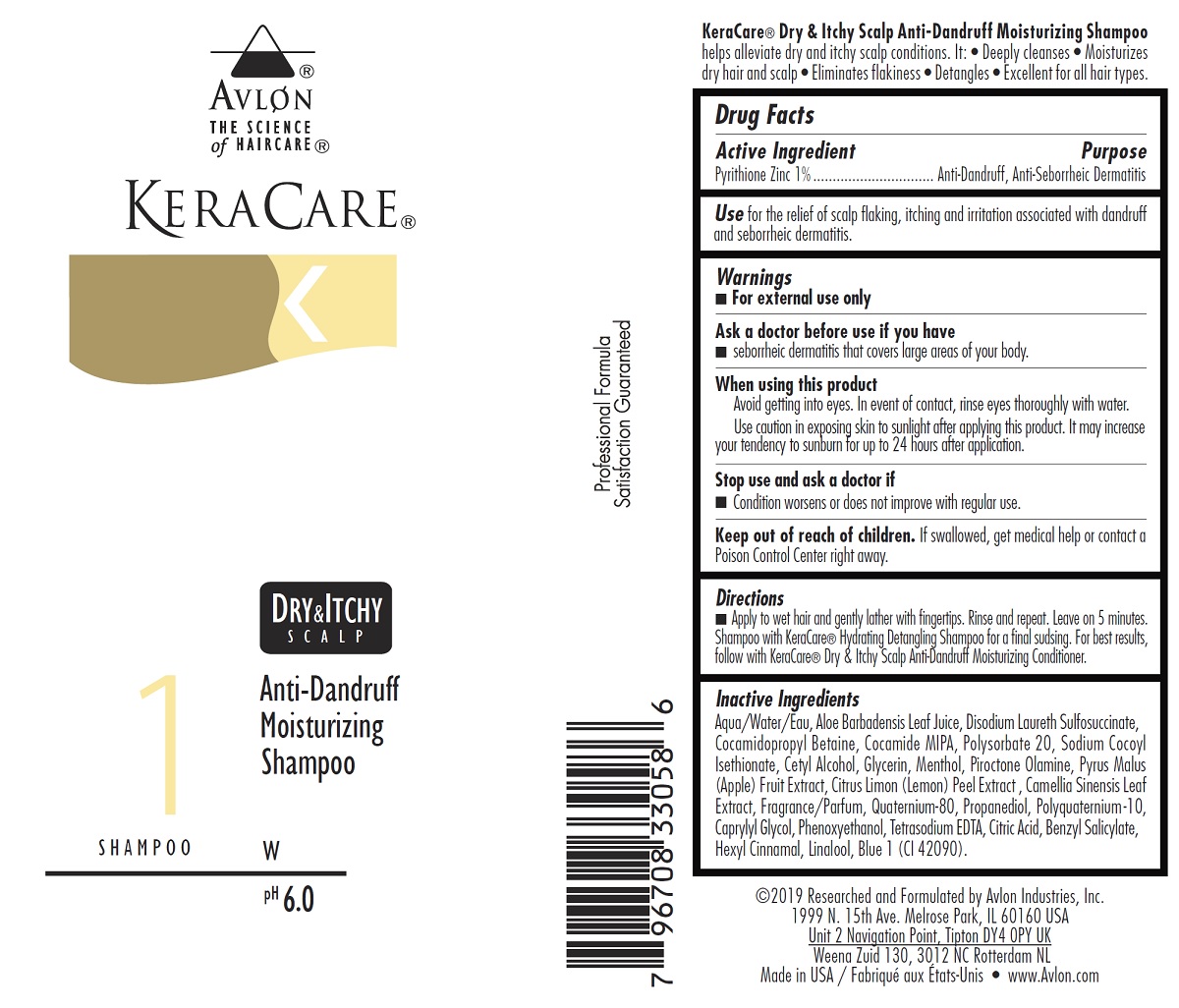 DRUG LABEL: KeraCare Dry and Itchy Scalp Anti-Dandruff
NDC: 63766-002 | Form: SHAMPOO
Manufacturer: Avlon Industries, Inc.
Category: otc | Type: HUMAN OTC DRUG LABEL
Date: 20241009

ACTIVE INGREDIENTS: PYRITHIONE ZINC 10 mg/1 mL
INACTIVE INGREDIENTS: LINALOOL, (+/-)-; WATER; ALOE VERA LEAF; DISODIUM LAURETH SULFOSUCCINATE; COCAMIDOPROPYL BETAINE; GLYCERIN; POLYSORBATE 20; SODIUM COCOYL ISETHIONATE; CAPRYLYL GLYCOL; COCO MONOISOPROPANOLAMIDE; CETYL ALCOHOL; APPLE; PROPANEDIOL; PHENOXYETHANOL; EDETATE SODIUM; .ALPHA.-HEXYLCINNAMALDEHYDE; MENTHOL; PIROCTONE OLAMINE; LEMON PEEL; GREEN TEA LEAF; FD&C BLUE NO. 1; CITRIC ACID MONOHYDRATE; BENZYL SALICYLATE; POLYQUATERNIUM-10 (30000 MPA.S AT 2%); 2-(CYCLOHEXYLAMINO)ETHANESULFONIC ACID

KeraCare Dry and Itchy Scalp Anti-Dandruff Moisturizing Shampoo

Active Ingredient

Pyrithione Zinc 1%

Purpose

Anti-Dandruff, Anti-Seborrheic Dermatitis

INDICATIONS AND USAGE

Use for the relief of scalp flaking, itching and irritation associated with

dandruff and seborrheic dermatitis.

Warnings

■ For external use only

-----------------------------------------------------------------------------------------------------

Ask a doctor before use if you have

■ seborrheic dermatitis that covers large areas of your body.

-----------------------------------------------------------------------------------------------------

When using this product

■ Avoid getting into eyes. In event of contact, rinse eyes thoroughly with water.

■ Use caution in exposing skin to sunlight after applying this product. It may

increase your tendency to sunburn for up to 24 hours after application.

-----------------------------------------------------------------------------------------------------

Stop use and ask a doctor if

■ Condition worsens or does not improve with regular use.

-----------------------------------------------------------------------------------------------------

Keep out of reach of children. If swallowed, get medical help or contact

a Poison Control Center right away.

Directions

- Apply to wet hair and gently lather with fingertips. Rinse and repeat. Leave on 5 minutes. Shampoo with KeraCare® Hydrating Detangling Shampoo for a final sudsing. For best results, follow with KeraCare® Dry & Itchy Scalp Anti-Dandruff Moisturizing Conditioner.

Inactive Ingredients

Aqua/Water/Eau, Aloe Barbadensis Leaf Juice, Disodium Laureth Sulfosuccinate,

Cocamidopropyl Betaine, Cocamide MIPA, Polysorbate 20, Sodium Cocoyl

Isethionate, Cetyl Alcohol, Glycerin, Menthol, Piroctone Olamine, Pyrus Malus

(Apple) Fruit Extract, Citrus Limon (Lemon) Peel Extract , Camellia Sinensis Leaf

Extract, Fragrance/Parfum, Quaternium-80, Propanediol, Polyquaternium-10,

Caprylyl Glycol, Phenoxyethanol, Tetrasodium EDTA, Citric Acid, Benzyl Salicylate,

Hexyl Cinnamal, Linalool, Blue 1 (CI 42090).

RECENT MAJOR CHANGES

Dosage and Administration Section

Section 9

10/2019

PACKAGE LABEL

KeraCare Dry and Itchy Scalp Anti-Dandruff Moisturizing Shampoo

Product NDC

63766-002